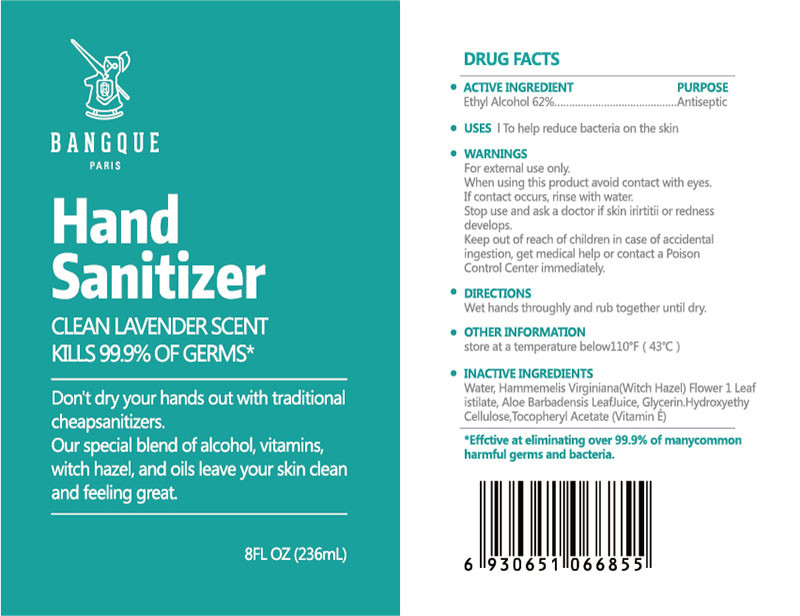 DRUG LABEL: HAND SANITIZER
NDC: 55415-002 | Form: LIQUID
Manufacturer: JIANGSU MEIFAN BIOTECHNOLOGY CO., LTD.
Category: otc | Type: HUMAN OTC DRUG LABEL
Date: 20240320

ACTIVE INGREDIENTS: ALCOHOL 146.32 mL/236 mL
INACTIVE INGREDIENTS: WATER; HAMAMELIS VIRGINIANA ROOT BARK/STEM BARK; ALOE VERA LEAF; GLYCERIN; .ALPHA.-TOCOPHEROL ACETATE; HYDROXYETHYL CELLULOSE, UNSPECIFIED

55415-02

DOSAGE AND ADMINISTRATION

store at a temperature below110*F (43°C)

INACTIVE INGREDIENT

Water, Hammemelis Virginiana (Witch Hazel) Flower, Leafistilate, Aloe Barbadensis Leaf Juice, Glycerin, Hydroxyethy Cellulose, Tocopheryl Acetate (Vitamin E)

INDICATIONS AND USAGE

Wet hands throughly and rub together until dry.

ACTIVE INGREDIENT

ETHYL ALCOHOL

keep out of children

PURPOSE

Disinfection
Sterilization
No Rinseing

WARNINGS

For extermal use only.When using this product avoid contact with eyes.If contact occurs, rinse with water.Stop use and ask a doctor if skin rirtiti or rednessdevelops.Keep out of reach of children in case of accidentalingestion, get medical help or contact a Poison Control Center immeditely.